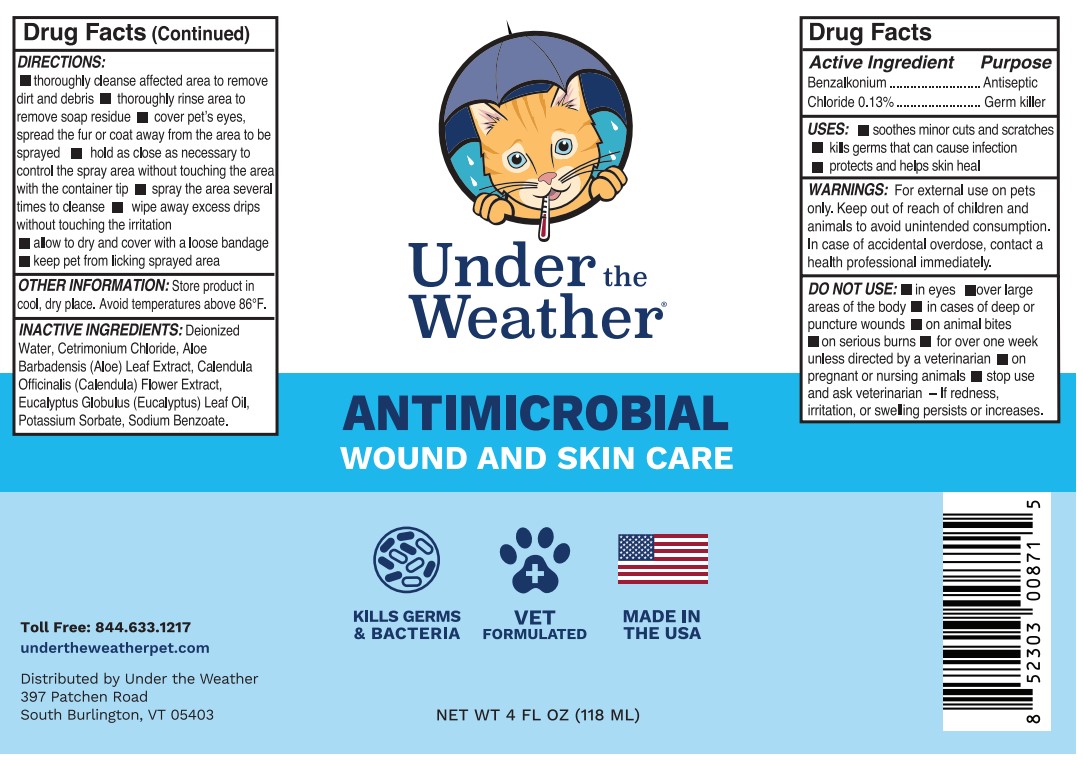 DRUG LABEL: ANTIMICROBIAL CAT
NDC: 86192-871 | Form: SOLUTION
Manufacturer: UNDER THE WEATHER
Category: animal | Type: OTC ANIMAL DRUG LABEL
Date: 20230815

ACTIVE INGREDIENTS: BENZALKONIUM CHLORIDE 13 g/100 mL
INACTIVE INGREDIENTS: WATER; CETRIMONIUM CHLORIDE; ALOE; CALENDULA OFFICINALIS FLOWER; EUCALYPTUS ALBA LEAF; POTASSIUM SORBATE; SODIUM BENZOATE

UNDER THE WEATHER ANTIMICROBIAL CAT

ACTIVE INGREDIENTS PER 4OZ BOTTLE

0.13 % BENZALKONIUM CHLORIDE

PURPOSE

ANTISEPTIC GERM KILLER

WARNINGS

FOR EXTERNAL USE ON PETS ONLY. KEEP OUT OF REACH OF CHILDREN AND ANIMALS TO AVOIDE UNINTENDED CONSUMPTION. IN CASE OF ACCIDENTAL OVERDOSE, CONTACT A HEALTH PROFESSIONAL IMMEDIATELY.